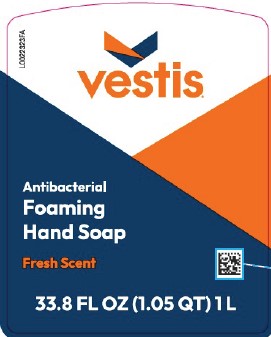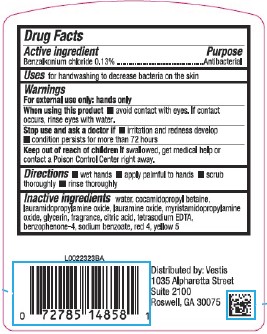 DRUG LABEL: Hand Wash
NDC: 71897-466 | Form: SOAP
Manufacturer: Veritiv Operating Company
Category: otc | Type: HUMAN OTC DRUG LABEL
Date: 20260216

ACTIVE INGREDIENTS: BENZALKONIUM CHLORIDE 1.3 mg/1 mL
INACTIVE INGREDIENTS: GLYCERIN; RED 4; YELLOW 5; LAURAMINE OXIDE; WATER; COCAMIDOPROPYL BETAINE; CITRIC ACID; TETRASODIUM EDTA; LAURAMIDOPROPYLAMINE OXIDE; MYRISTAMIDOPROPYLAMINE OXIDE; SODIUM BENZOATE; BENZOPHENONE-4

Vestis 466.001/466AC
Antibacterial Foaming Hand Wash

Active Ingredient

Benzalkonium chloride 0.13%

Purpose

Antibacterial

Uses

for handwashing to decrease bacteria on the skin

Warnings

For external use only: hands only

When using this product

- avoid contact with eyes. If contact occurs, rinse eyes with water.

Stop use and ask a doctor if

- irritation and redness develop
- condition persists for more than 72 hours

Keep out of reach of children.

If swallowed, get medical help or contact a Poison Control Center right away.

Directions

- wet hands
- apply palmful to hands
- scrub thoroughly
- rinse thoroughly

Inactive Ingredients

water, cocamidopropyl betaine, lauramidopropylamine oxide, lauramine oxide, myristamidopropylamine oxide, glycerin, fragrance, citric acid, tetrasodium EDTA, benzophenone-4, sodium benzoate, red 4, yellow 5

Adverse Reaction

Distributed by: Vestis

1035 Alpharetta Street

Suite 2100

Roswell, GA 30075

Principal Display Panel

vestis®

Antibacterial

Foaming

Hand Soap

Fresh Scent

33.8 FL OZ (1.05 QT) 1 L